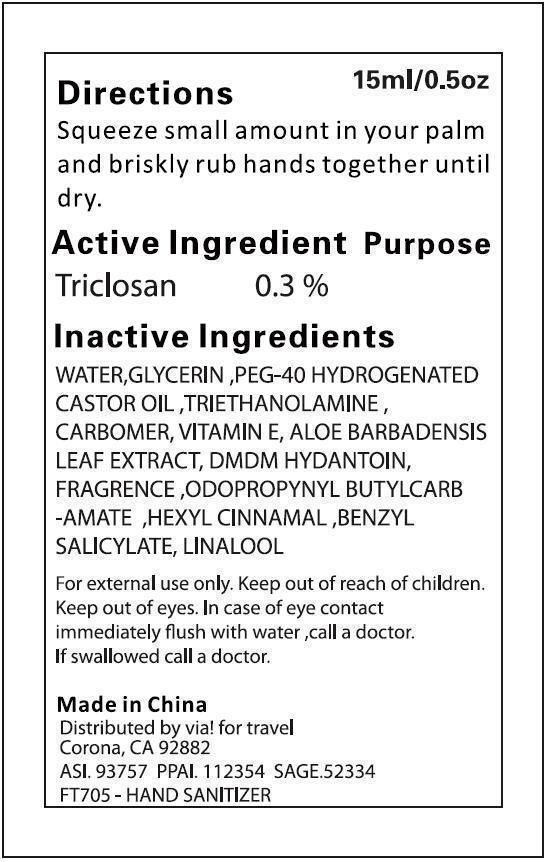 DRUG LABEL: ALCOHOL FREE HAND SANITIZER
NDC: 47993-230 | Form: LIQUID
Manufacturer: NINGBO JIANGBEI OCEAN STAR TRADING CO.,LTD
Category: otc | Type: HUMAN OTC DRUG LABEL
Date: 20150212

ACTIVE INGREDIENTS: TRICLOSAN 0.3 g/100 g
INACTIVE INGREDIENTS: WATER 96.4501 g/100 g; GLYCERIN 2 g/100 g; PEG-40 HYDROGENATED LANOLIN 0.5 g/100 g; TROLAMINE 0.2 g/100 g; CARBOMER 940 0.2 g/100 g; TOCOPHEROL 0.05 g/100 g; ALOE VERA LEAF 0.1 g/100 g; DMDM HYDANTOIN 0.15 g/100 g; AROMADENDRIN 0.03 g/100 g; IODOPROPYNYL BUTYLCARBAMATE 0.0075 g/100 g; CYCLOHEXYL CINNAMATE 0.009 g/100 g; BENZYL SALICYLATE 0.00162 g/100 g; 3,7-DIMETHYL-1-OCTANOL 0.0018 g/100 g

Active Ingredients

Active ingredients--------------purpose

Ethyl Alcohol 62%------------antiseptic

Uses:
Reduces bacteria on the skin. Recommended for repeated use.

Warnings:

For external use only.Flammable:Keep away from heat for flame.Do no use in or near the eyes. In case of contact, rinse eyes thoroughly with water.

Directions:

Place enough product in your palm to thoroughly cover your hands. Rub hands together briskly until dry.

Other Information

Do not store above 110F(43C) May discolor certain fabric or surfaces. Harmful to wood finishes and plastics.

KEEP OUT OF REACH OF CHILDREN

Children under 6 years of age should be super vised when using this product.

Inactive Ingredients:

Water,Glycerin,Isopropyl Myristate, Propylene Glycol,Tocopheryl Acetate, Aminomethyl Propanol, Carbomer, Fragrance